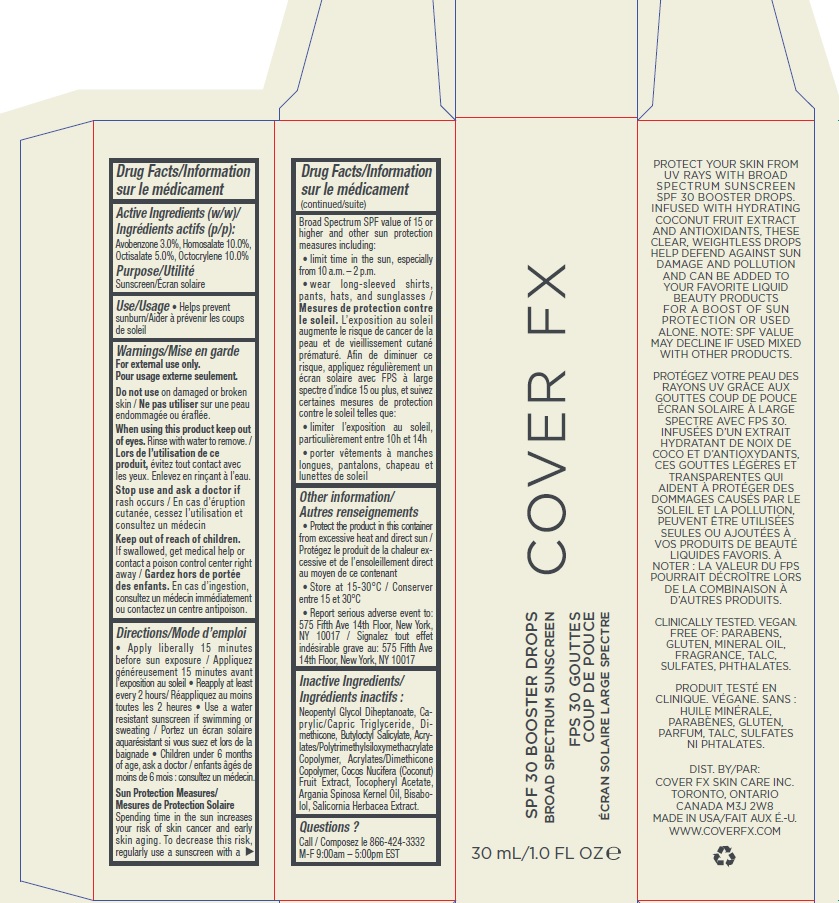 DRUG LABEL: COVER FX SPF 30 BOOSTER DROPS BROAD SPECTRUM SUNSCREEN
NDC: 68327-074 | Form: OIL
Manufacturer: Cover FX Skin Care Inc.
Category: otc | Type: HUMAN OTC DRUG LABEL
Date: 20190123

ACTIVE INGREDIENTS: HOMOSALATE 100 mg/1 mL; OCTISALATE 50 mg/1 mL; AVOBENZONE 30 mg/1 mL; OCTOCRYLENE 100 mg/1 mL
INACTIVE INGREDIENTS: SALICORNIA EUROPAEA; ARGAN OIL; LEVOMENOL; ALPHA-TOCOPHEROL ACETATE; MEDIUM-CHAIN TRIGLYCERIDES; DIMETHICONE; NEOPENTYL GLYCOL DIHEPTANOATE; BUTYLOCTYL SALICYLATE; COCONUT

COVER FX SPF 30 BOOSTER DROPS BROAD SPECTRUM SUNSCREEN

Active Ingredients

Avobenzone 3.0%

Homosalate 10.0%

Octisalate 5.0%

Octocrylene 10.0%

Purpose: Sunscreen

Use

Helps prevent sunburn

Warnings

For external use only.

Do not use on damaged or broken skin.

When using this product keep out of eyes. Rinse with water to remove.

Stop use and ask a doctor if rash occurs.

KEEP OUT OF REACH OF CHILDREN

Keep out of the reach of children. If swallowed, get medical help or contact a poison control center right away.

Directions

Apply liberally 15 minutes before sun exposure.

Reapply at least every 2 hours.

Use a water resistant sunscreen if swimming or sweating.

Children under 6 months of age, ask a doctor.

Sun Protection Measures. Spending time in the sun increases your risk of skin cancer and early skin aging. To decrease this risk, regularly use a sunscreen with a Broad Spectrum SPF value of 15 or higher and other sun protection measures including:

- limit time in the sun, especially from 10 a.m.-2 p.m.
- wear long-sleeved shirts, pants, hats and sunglasses.

Other information

Protect the product in this container from excessive heat and direct sun

Store at 15 – 30 °C

Report serious adverse event to: 575 Fifth Ave 14th Floor, New York, NY10017

Inactive ingredients

Neopentyl Glycol Diheptanoate, Caprylic/Capric Triglyceride, Dimethicone, Butyloctyl Salicylate, Acrylates/Polytrimethylsiloxymethacrylate Copolymer, Acrylates/Dimethicone Copolymer, Cocos Nucifera (Coconut) Fruit Extract, Tocopheryl Acetate, Argania Spinosa Kernel Oil, Bisabolol, Salicornia Herbacea Extract.

Questions?

Call 866-424-3332 M-F 9:00am – 5:00pm EST

Company information

DIST BY COVER FX SKIN CARE INC.

TORONTO, ONTARIO CANADA M3J 2W8

MADE IN USA

WWW.COVERFX.COM

Product Packaging

COVER FX

SPF 30 BOOSTER DROPS

BROAD SPECTRUM SUNSCREEN

30 mL/1.0 FL OZ